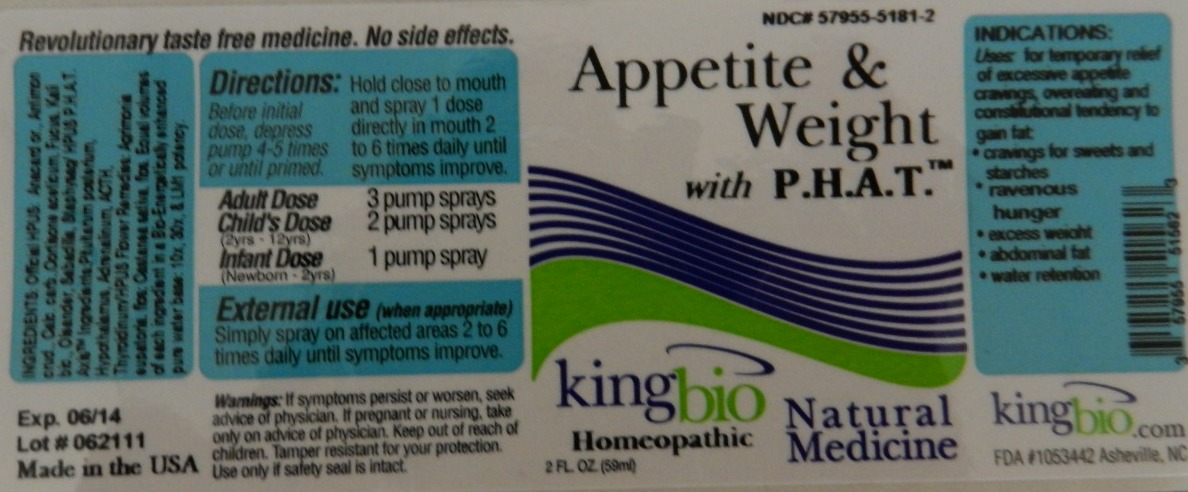 DRUG LABEL: Appetite and Weight with P.H.A.T.
NDC: 57955-5181 | Form: LIQUID
Manufacturer: King Bio Inc.
Category: homeopathic | Type: HUMAN OTC DRUG LABEL
Date: 20110615

ACTIVE INGREDIENTS: SEMECARPUS ANACARDIUM JUICE 10 [hp_X]/1 mL; ANTIMONY TRISULFIDE 10 [hp_X]/1 mL; OYSTER SHELL CALCIUM CARBONATE, CRUDE 10 [hp_X]/1 mL; CORTISONE ACETATE 10 [hp_X]/1 mL; FUCUS VESICULOSUS 10 [hp_X]/1 mL; POTASSIUM DICHROMATE 10 [hp_X]/1 mL; NERIUM OLEANDER LEAF 10 [hp_X]/1 mL; SCHOENOCAULON OFFICINALE SEED 10 [hp_X]/1 mL; DELPHINIUM STAPHISAGRIA SEED 10 [hp_X]/1 mL; CORTICOTROPIN 10 [hp_X]/1 mL; THYROID 10 [hp_X]/1 mL; AGRIMONIA EUPATORIA FLOWER 10 [hp_X]/1 mL; CASTANEA SATIVA FLOWER 10 [hp_X]/1 mL; SUS SCROFA PITUITARY GLAND 10 [hp_X]/1 mL; BOS TAURUS HYPOTHALAMUS 10 [hp_X]/1 mL; EPINEPHRINE 10 [hp_X]/1 mL
INACTIVE INGREDIENTS: WATER

Appetite and Weight with P.H.A.T.

Active Ingredients

Ingredients: Official HPUS:

Anacardium Orientale

Antimonium Crudum

Calcarea Carbonica

Cortisone Aceticum

Fucus Vesiculosus

Kali Bichromicum

Oleander

Sabadilla

Staphysagria

HPUS: P.H.A.T. Axis Ingredients:

Pituitarum Posterionum

Hypothalamus

Adrenalinum

ACTH

Thyroidinum

HPUS Flower Remedies:

Agrimonia Eupatoria, flos.

Castanea Sativa, flos.

Referenced to image: appetite and weight.jpg

Inactive Ingredient

Bio-Energetically enhanced pure water base

Referenced to image: appetite and weight.jpg

Dosage and Administration

Direction: Hold close to mouth and spray 1 dose directly into mouth 2 to 6 times daily until symptoms improve.

Adult Dose: 3 pump sprays

Child's Dose: 2 pump sprays (2yrs to 12 yrs)

Infant Dose: 1 pump sprays (newborn to 2 yrs)

External use: (when appropriate) Simply spray on affected areas 2 to 6 times daily until symptoms improve.

Referenced to image: appetite and weight.jpg

OTC Purpose section

Indications: Uses for temporary relief of excessive appetite cravings, overeating and constitutional tendency to gain fat:

- cravings for sweets and starches
- ravenous hunger
- excess weight
- abdominal fat
- water retention

Referenced to image: appetite and weight.jpg

Warnings

Warnings: If symptoms persist or worsen, seek advice of physician. If pregnant or nursing, take only on advice of physician. Keep out of reach of children. Tamper resistant for your protection. Use only if safety seal is intact.

Referenced to image: appetite and weight.jpg

OTC Keep out of reach children section

Keep out of reach of children.

Referenced to image: appetite and weight.jpg

Indications and Usage Section

Uses for temporary relief of excessive appetite cravings, overeating and constitutional tendency to gain fat, cravings for sweets and starches, ravenous hunger, excess weight, abdominal fat, water retention.

Referenced to image: appetite and weight.jpg

PACKAGE LABEL

Referenced to image: appetite and weight.jpg